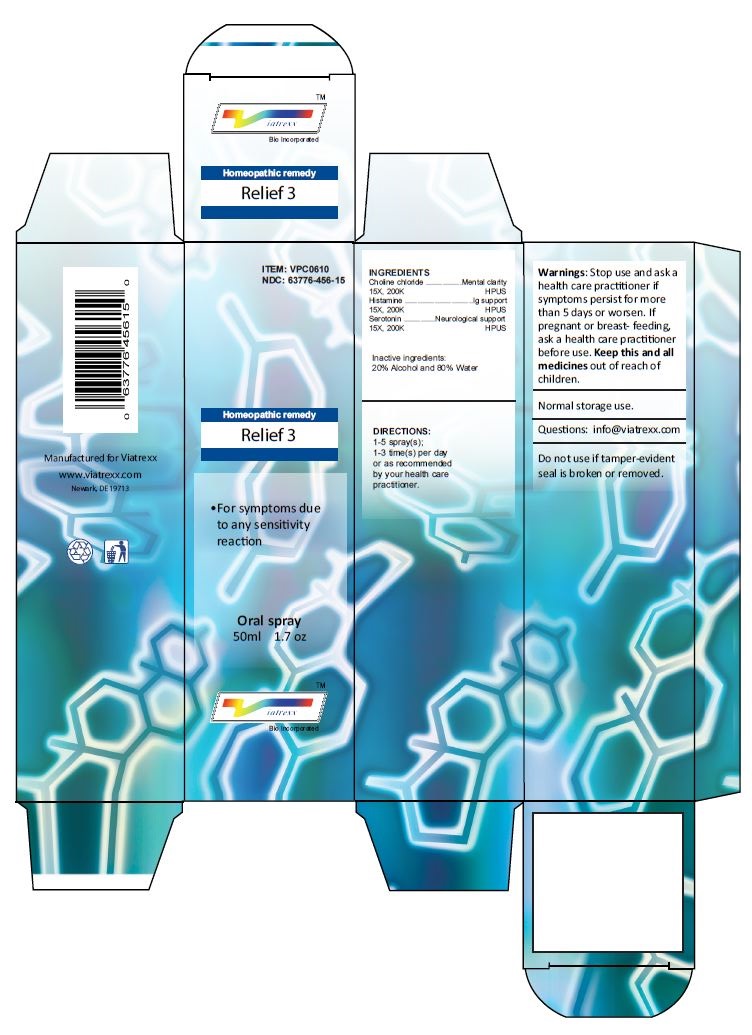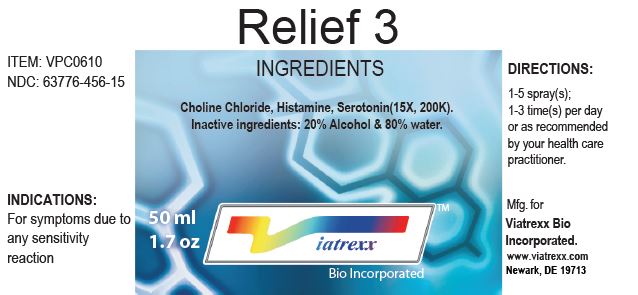 DRUG LABEL: Relief 3
NDC: 63776-456 | Form: SPRAY
Manufacturer: VIATREXX BIO INCORPORATED
Category: homeopathic | Type: HUMAN OTC DRUG LABEL
Date: 20181005

ACTIVE INGREDIENTS: Choline Chloride 200 [kp_C]/1 mL; Histamine 200 [kp_C]/1 mL; Serotonin 200 [kp_C]/1 mL
INACTIVE INGREDIENTS: Alcohol; Water

Relief 3

Purpose:

Choline chloride | Mental clarity
Histamine | IG support
Serotonin | Neurological support

INDICATIONS AND USAGE

● For symptoms due to any sensitivity reaction

INGREDIENTS

Choline chloride 15X 200K HPUS, Histamine 15X 200K HPUS, Serotonin 15X 200K HPUS

Inactive ingredients:
20% Alcohol and 80% Water

DIRECTIONS:

1-5 spray(s); 1-3 time(s) per day or as recommended by your health care practitioner.

WARNINGS

Warnings: Stop use and ask a health care practitioner if symptoms persist for more than 5 days or worsen. If pregnant or breast- feeding, ask a health care practitioner before use.

KEEP OUT OF REACH OF CHILDREN

Keep this and all medicines out of reach of children.

Normal storage use.

Questions: info@viatrexx.com

Do not use if tamper-evident seal is broken or removed.

Principal Display Panel

ITEM: VPC0610
NDC 63776-456-15
Homeopathic remedy
Relief 3
• For symptoms due to any sensitivity reaction
Oral spray
50ml 1.7 oz
Viatrexx™ Bio Incorporated
Manufactured for Viatrexx
www.viatrexx.com
Newark, DE 19713

Relief 3
INGREDIENTS
Choline Chloride, Histamine, Serotonin(15X, 200K).
Inactive ingredients: 20% Alcohol & 80% water.
50 ml
1.7 oz
Viatrexx™ Bio Incorporated
ITEM: VPC0610
NDC: 63776-456-15
INDICATIONS:
For symptoms due to any sensitivity reaction
DIRECTIONS:
1-5 spray(s); 1-3 time(s) per day or as recommended by your health care practitioner.
Mfg. for
Viatrexx Bio Incorporated.
www.viatrexx.com
Newark, DE 19713